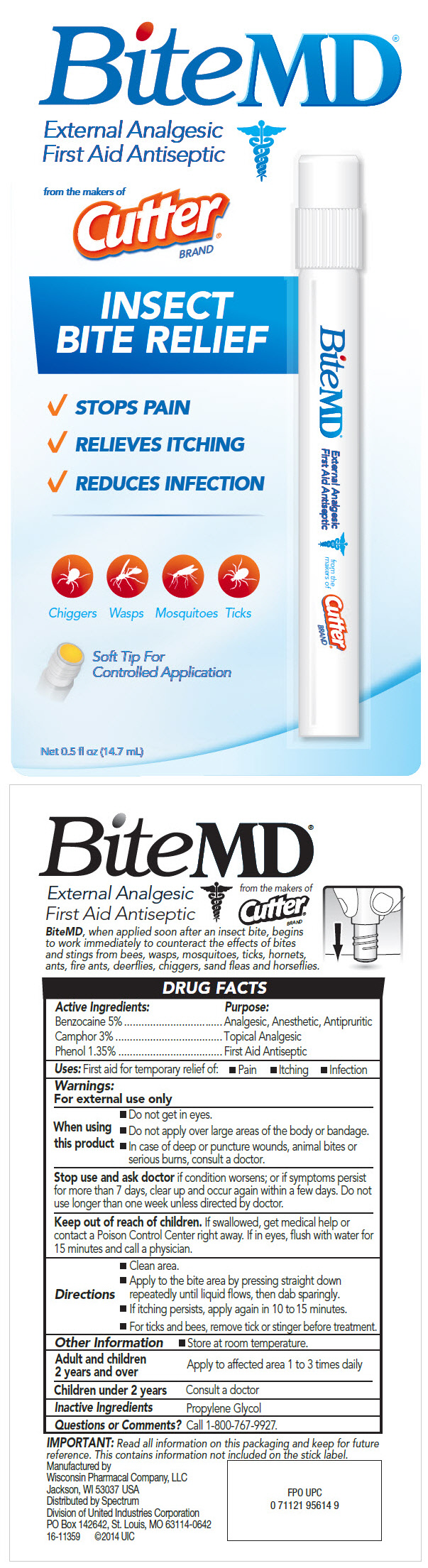 DRUG LABEL: BiteMD External Analgesic First Aid Antiseptic
NDC: 79364-0932 | Form: LIQUID
Manufacturer: United Industries Corporation
Category: otc | Type: HUMAN OTC DRUG LABEL
Date: 20241223

ACTIVE INGREDIENTS: Benzocaine 0.0524 mg/1 mL; CAMPHOR (SYNTHETIC) 0.03144 mg/1 mL; Phenol 0.01572 mg/1 mL
INACTIVE INGREDIENTS: Propylene Glycol

BiteMD® External Analgesic First Aid Antiseptic

DRUG FACTS

ACTIVE INGREDIENT

Active Ingredients: | Purpose:
Benzocaine 5% | Analgesic, Anesthetic, Antipruritic
Camphor 3% | Topical Analgesic
Phenol 1.35% | First Aid Antiseptic

Uses

First aid for temporary relief of:

- Pain
- Itching
- Infection

Warnings

For external use only

When using this product

- Do not get in eyes.
- Do not apply over large areas of the body or bandage.
- In case of deep or puncture wounds, animal bites or serious burns, consult a doctor.

Stop use and ask doctor if condition worsens; or if symptoms persist for more than 7 days, clear up and occur again within a few days. Do not use longer than one week unless directed by doctor.

Keep out of reach of children. If swallowed, get medical help or contact a Poison Control Center right away. If in eyes, flush with water for 15 minutes and call a physician.

Directions

- Clean area.
- Apply to the bite area by pressing straight down repeatedly until liquid flows, then dab sparingly.
- If itching persists, apply again in 10 to 15 minutes.
- For ticks and bees, remove tick or stinger before treatment.

Other Information

- Store at room temperature.

Adult and children 2 years and over

Apply to affected area 1 to 3 times daily

Children under 2 years

Consult a doctor

Inactive Ingredients

Propylene Glycol

Questions or Comments?

Call 1-800-767-9927.

Manufactured by
Wisconsin Pharmacal Company, LLC
Jackson, WI 53037 USA
Distributed by Spectrum
Division of United Industries Corporation
PO Box 142642, St. Louis, MO 63114-0642

PRINCIPAL DISPLAY PANEL - 14.7 mL Bottle Label

BiteMD®

External Analgesic
First Aid Antiseptic

from the makers of
Cutter®
BRAND

INSECT
BITE RELIEF

✓ STOPS PAIN
✓ RELIEVES ITCHING
✓ REDUCES INFECTION

Chiggers
Wasps
Mosquitoes
Ticks

Soft Tip For
Controlled Application

Net 0.5 fl oz (14.7 mL)